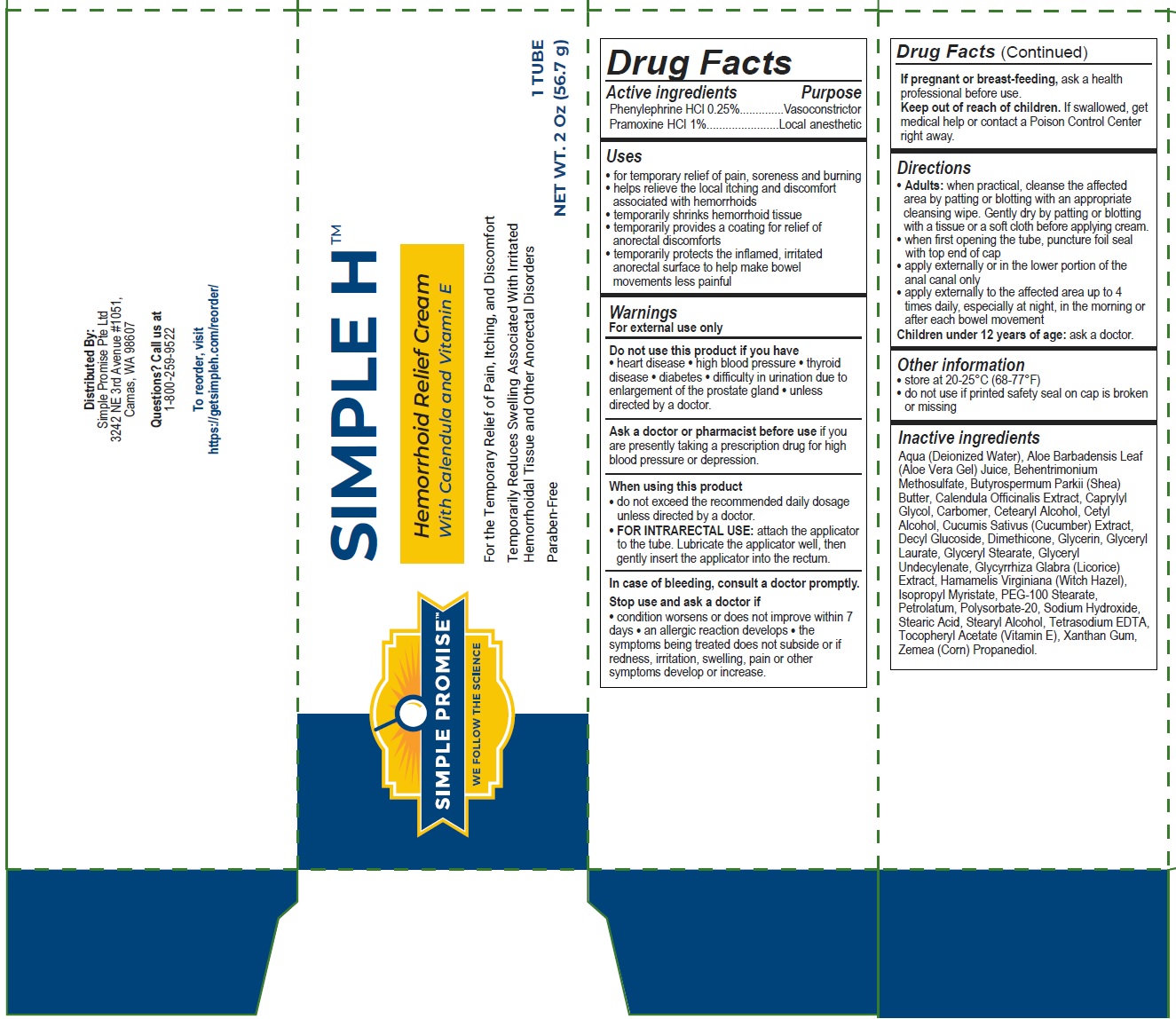 DRUG LABEL: SIMPLE PROMISE Simple H Hemorrhoid Relief Cream
NDC: 83311-335 | Form: CREAM
Manufacturer: SIMPLE PROMISE PTE LTD
Category: otc | Type: HUMAN OTC DRUG LABEL
Date: 20231106

ACTIVE INGREDIENTS: PHENYLEPHRINE HYDROCHLORIDE 2.5 mg/1 g; PRAMOXINE HYDROCHLORIDE 10 mg/1 g
INACTIVE INGREDIENTS: WATER; ALOE VERA LEAF; BEHENTRIMONIUM METHOSULFATE; SHEA BUTTER; CALENDULA OFFICINALIS FLOWER; CAPRYLYL GLYCOL; CARBOMER HOMOPOLYMER, UNSPECIFIED TYPE; CETOSTEARYL ALCOHOL; CETYL ALCOHOL; CUCUMBER; DECYL GLUCOSIDE; DIMETHICONE; GLYCERIN; GLYCERYL LAURATE; GLYCERYL MONOSTEARATE; GLYCYRRHIZA GLABRA; HAMAMELIS VIRGINIANA ROOT BARK/STEM BARK; ISOPROPYL MYRISTATE; PEG-100 STEARATE; PETROLATUM; POLYSORBATE 20; SODIUM HYDROXIDE; STEARIC ACID; STEARYL ALCOHOL; EDETATE SODIUM; .ALPHA.-TOCOPHEROL ACETATE; XANTHAN GUM; CORN; PROPANEDIOL

SIMPLE PROMISE Simple H Hemorrhoid Relief Cream

Active ingredients

Phenylephrine HCl 0.25%

Pramoxine HCl 1%

Purpose

Vasoconstrictor

Local anesthetic

Uses

• for temporary relief of pain, soreness and burning • helps relieve the local itching and discomfort associated with hemorrhoids • temporarily shrinks hemorrhoid tissue • temporarily provides a coating for relief of anorectal discomforts • temporarily protects the inflamed, irritated anorectal surface to help make bowel movements less painful

Warnings

For external use only

Do not use

this product if you have

• heart disease • high blood pressure • thyroid disease • diabetes • difficulty in urination due to enlargement of the prostate gland • unless directed by a doctor.

Ask a doctor or pharmacist before use

if you are presently taking a prescription drug for high blood pressure or depression.

When using this product

• do not exceed the recommended daily dosage unless directed by a doctor.

• attach the applicator to the tube. Lubricate the applicator well, then gently insert the applicator into the rectum. FOR INTRARECTAL USE:

In case of bleeding, consult a doctor promptly.

Stop use and ask a doctor if

• condition worsens or does not improve within 7 days • an allergic reaction develops • the symptoms being treated does not subside or if redness, irritation, swelling, pain or other symptoms develop or increase.

If pregnant or breast-feeding,

ask a health professional before use.

Keep out of reach of children.

If swallowed, get medical help or contact a Poison Control Center right away.

Directions

• : when practical, cleanse the affected area by patting or blotting with an appropriate cleansing wipe. Gently dry by patting or blotting with a tissue or a soft cloth before applying cream. • when first opening the tube, puncture foil seal with top end of cap • apply externally or in the lower portion of the anal canal only • apply externally to the affected area up to 4 times daily, especially at night, in the morning or after each bowel movement Children under 12 years of age: ask a doctor. Adults

Other information

• store at 20-25°C (68-77°F) • do not use if printed safety seal on cap is broken or missing

Inactive ingredients

Aqua (Deionized Water), Aloe Barbadensis Leaf (Aloe Vera Gel) Juice, Behentrimonium Methosulfate, Butyrospermum Parkii (Shea) Butter, Calendula Officinalis Extract, Caprylyl Glycol, Carbomer, Cetearyl Alcohol, Cetyl Alcohol, Cucumis Sativus (Cucumber) Extract, Decyl Glucoside, Dimethicone, Glycerin, Glyceryl Laurate, Glyceryl Stearate, Glyceryl Undecylenate, Glycyrrhiza Glabra (Licorice) Extract, Hamamelis Virginiana (Witch Hazel), Isopropyl Myristate, PEG-100 Stearate, Petrolatum, Polysorbate-20, Sodium Hydroxide, Stearic Acid, Stearyl Alcohol, Tetrasodium EDTA, Tocopheryl Acetate (Vitamin E), Xanthan Gum, Zemea (Corn) Propanediol.